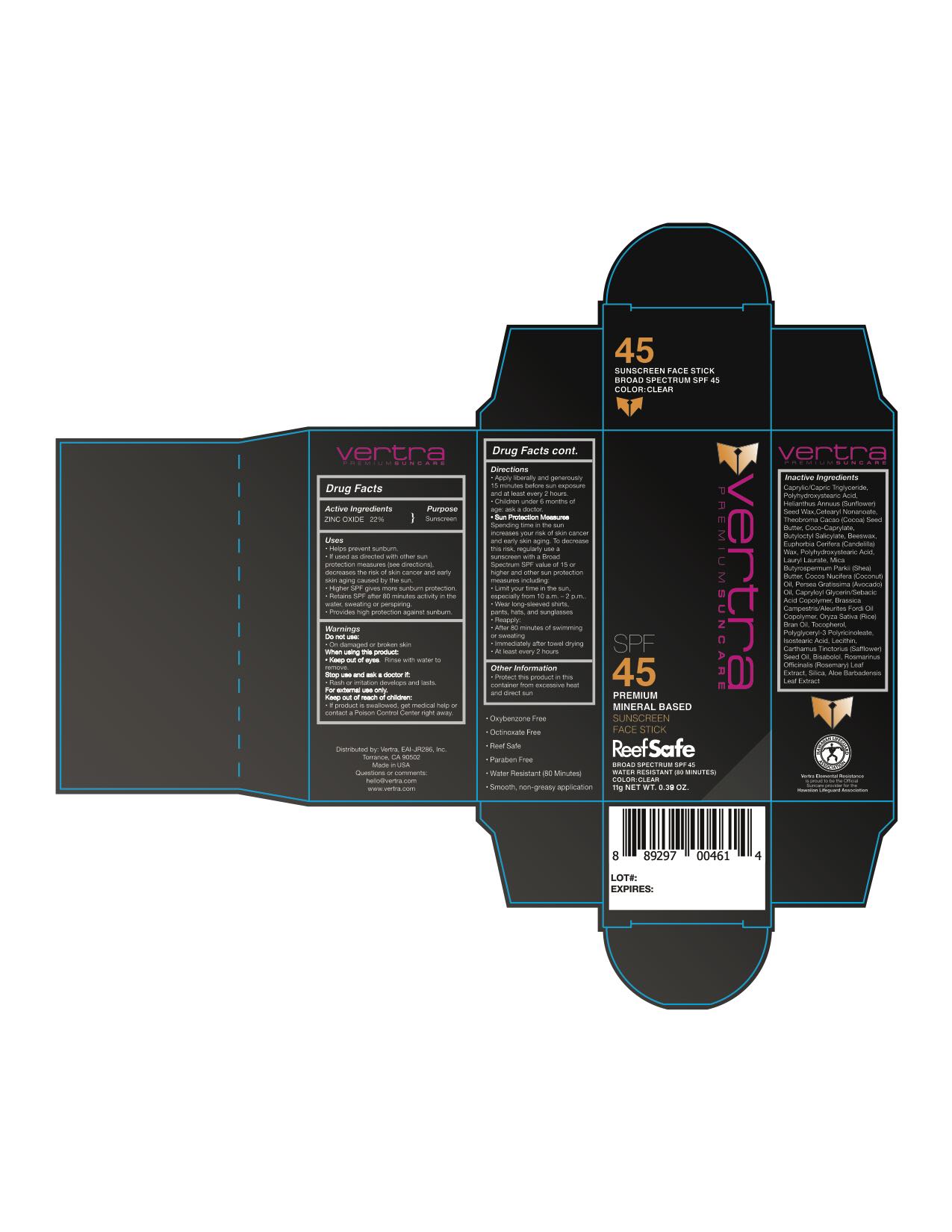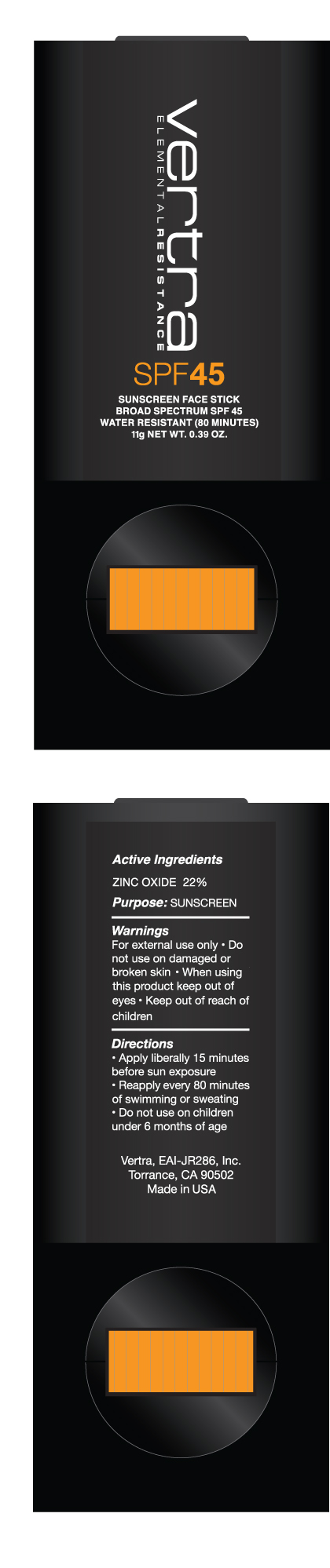 DRUG LABEL: Clear Suncreen Face Stick Broad Spectrum SPF 45
NDC: 71014-019 | Form: STICK
Manufacturer: Eai-jr 286, Inc
Category: otc | Type: HUMAN OTC DRUG LABEL
Date: 20200813

ACTIVE INGREDIENTS: ZINC OXIDE 22 g/100 g
INACTIVE INGREDIENTS: TOCOPHEROL; POLYHYDROXYSTEARIC ACID (2300 MW); MEDIUM-CHAIN TRIGLYCERIDES; LECITHIN, SOYBEAN; STEARIC ACID; HELIANTHUS ANNUUS SEED WAX; CETEARYL NONANOATE; COCOA BUTTER; BUTYLOCTYL SALICYLATE; YELLOW WAX; CANDELILLA WAX; LAURYL LAURATE; MICA; SHEA BUTTER; COCO-CAPRYLATE; COCONUT OIL; AVOCADO OIL; CAPRYLOYL GLYCERIN/SEBACIC ACID COPOLYMER (2000 MPA.S); RICE BRAN OIL; POLYGLYCERYL-3 PENTARICINOLEATE; ISOSTEARIC ACID; SAFFLOWER OIL; LEVOMENOL; ROSEMARY; SILICON DIOXIDE; ALOE VERA LEAF

Vertra Clear Foundation Sunscreen Face Stick Broad Spectrum SPF 45

Active Ingredients Purpose

Zinc Oxide 22% Sunscreen

PURPOSE

- helps prevent sunburn
- if used as directed with other sun protection measures (see Directions), decreases the risk of skin cancer and early skin aging caused by the sun
- Higher SPF gives more sunburn protection
- Retains SPF after 80 minutes activity in the water, sweating, or perspiring.
- Provides high protection against sunburn

Keep out of reach of children:

If product is swallowed, get medical help or contact a Poison Control Center right away.

Warnings

For external use only

Do not use on damaged or broken skin
When using this product: keep out of eyes
Rinse with water to remove

Directions

apply liberally and evenly 15 minutes before sun exposure and and at least every 2 hours
reapply: after 80 minutes of swimming or sweating

children under 6 months of age: ask a doctor

Sun Protection Measures. Spending time in the sun increases your risk of skin cancer and early skin aging. To decrease this risk, regularly use a sunscreen with a Broad Spectrum SPF value 15 or higher and other sun protection measures including:
limit time in the sun, especially from 10 a.m. - 2 p.m.
wear long-sleeve shirts, pants, hats, and sunglasses
immediately after towel drying

Stop use and ask a doctor if:

rash or irritation develops and lasts

Inactive Ingredients

Caprylic/Capric Triglyceride, Polyhydroxystearic Acid, Helianthus Annuus (Sunflower) Seed Wax, Cetearyl Nonanoate, Theobroma Cacao (Cacao) Seed Butter, Coco-Caprylate, Butyloctyl Salicylate, Beeswax, Euphorbia Cerifera (Candelilla) Wax, polyhydroxystearic Acid, Lauryl Laurate, Mica, Butyrospermum Parkii (Shea) Butter, Cocos Nucifera (Coconut) Oil, Persea Gratissima (Avocado) Oil, Capryloyl Glycerin/Sebacic Acid Copolymer, Brassica Campestris/Aleurites Fordi Oil Copolymer, Oryza Sativa (Rice) Brain Oil, Tocopherol, Polyglyceryl-3 Polyricinoleate, Isostearic Acid, Lecithin, Carthamus Tinctorius (Safflower) Seed Oil, Bisabolol, Rosmarinus Officinalis (Rosemary) Leaf Extract, Silica, Aloe Barbadensis Leaf Extract

PACKAGE LABEL

Vertra Premium Sunscreen

SPF 45

Premium Mineral Based

Sunscreen Face Stick

Broad Spectrum SPF 45

Water Resistant (80 Minutes)

Color: Clear

11g NET WT. 0.39 OZ